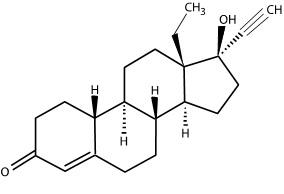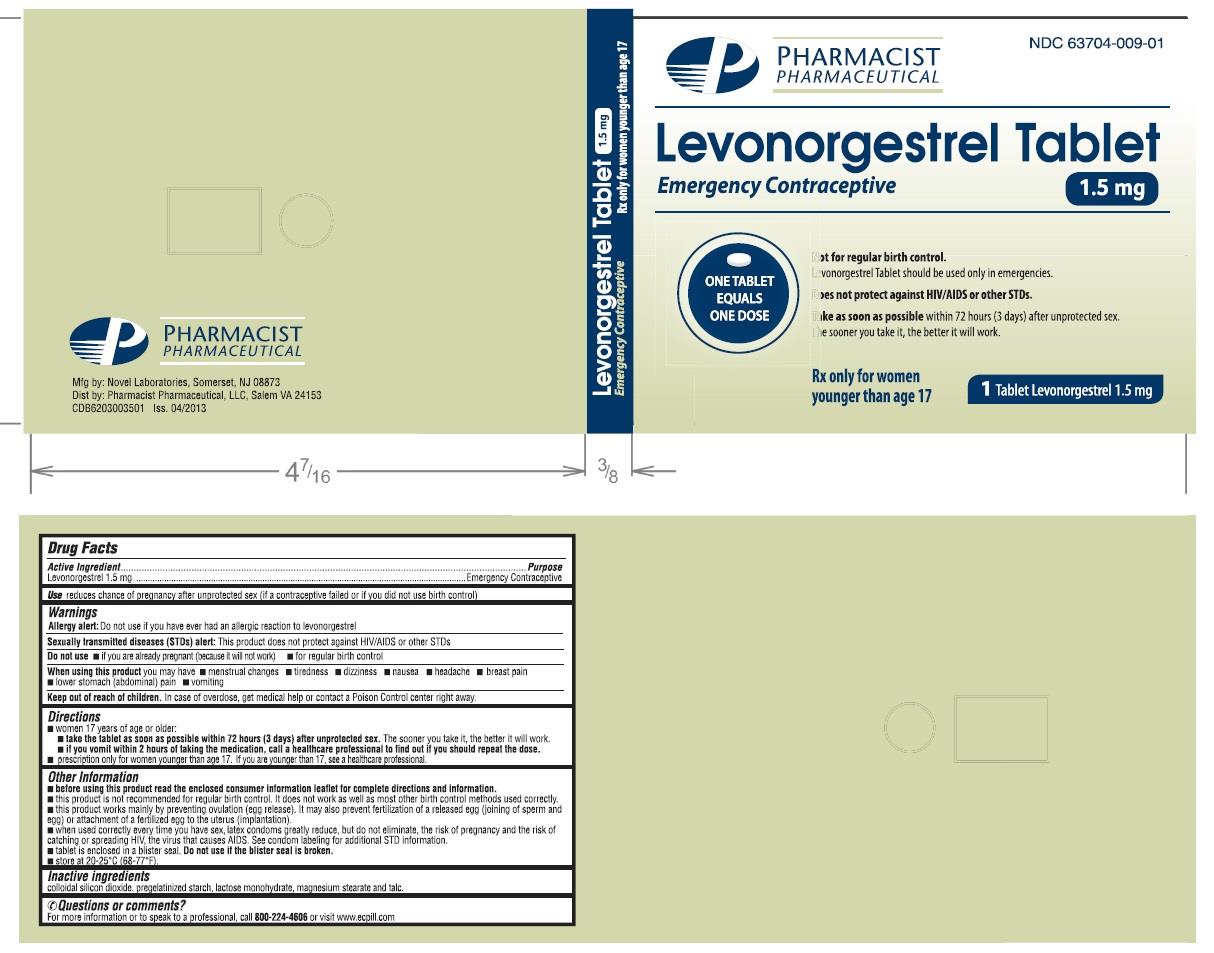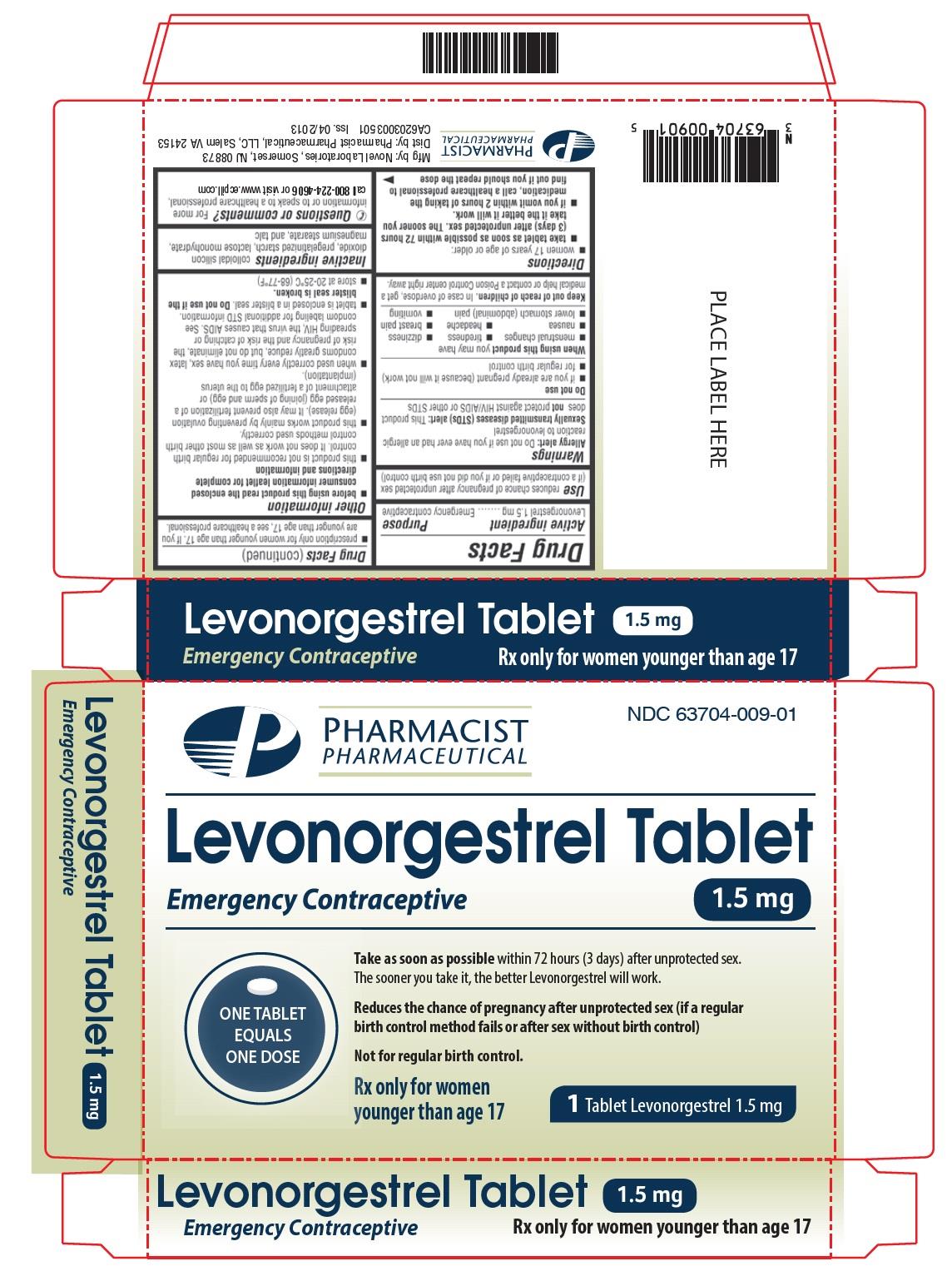 DRUG LABEL: Levonorgestrel
NDC: 63704-009 | Form: TABLET
Manufacturer: Pharmacist Pharmaceutical, LLC
Category: prescription | Type: HUMAN PRESCRIPTION DRUG LABEL
Date: 20130729

ACTIVE INGREDIENTS: LEVONORGESTREL 1.5 mg/1 1
INACTIVE INGREDIENTS: SILICON DIOXIDE; STARCH, CORN; LACTOSE MONOHYDRATE; MAGNESIUM STEARATE; TALC

HIGHLIGHTS OF PRESCRIBING INFORMATION

These highlights do not include all the information needed to use Levonorgestrel safely and effectively. See full prescribing information for Levonorgestrel.
Levonorgestrel (Levonorgestrel) TABLET for ORAL use.
Initial U.S. Approval: 1982

1 INDICATIONS & USAGE

Levonorgestrel Tablet is a progestin-only emergency contraceptive indicated for prevention of pregnancy following unprotected intercourse or a known or suspected contraceptive failure. Levonorgestrel Tablet is available only by prescription for women younger than age 17 years, and available over the counter for women 17 years and older. Levonorgestrel Tablet is not intended for routine use as a contraceptive. (1)

2 DOSAGE & ADMINISTRATION

One tablet taken orally as soon as possible within 72 hours after unprotected intercourse. Efficacy is better if the tablet is taken as soon as possible after unprotected intercourse. (2)

3 DOSAGE FORMS & STRENGTHS

1.5 mg tablet (3)

4 CONTRAINDICATIONS

Known or suspected pregnancy (4)

5 WARNINGS AND PRECAUTIONS

- Ectopic pregnancy: Women who become pregnant or complain of lower abdominal pain after taking Levonorgestrel Tablet should be evaluated for ectopic pregnancy. (5.1)
- Levonorgestrel Tablet is not effective in terminating an existing pregnancy. (5.2)
- Effect on menses: Levonorgestrel Tablet may alter the next expected menses. If menses is delayed beyond 1 week, pregnancy should be considered. (5.3)
- STI/HIV: Levonorgestrel Tablet does not protect against STI/HIV. (5.4)

6 ADVERSE REACTIONS

The most common adverse reactions (≥10%) in clinical trials included heavier menstrual bleeding (31%), nausea (14%), lower abdominal pain (13%), fatigue (13%), headache (10%), and dizziness (10%). (6.1)

To report SUSPECTED ADVERSE REACTIONS, contact at or FDA at 1-800-FDA-1088 or www.fda.gov/medwatch.

7 DRUG INTERACTIONS

Drugs or herbal products that induce certain enzymes, such as CYP3A4, may decrease the effectiveness of progestin-only pills. (7)

8 USE IN SPECIFIC POPULATIONS

- Nursing Mothers: Small amounts of progestin pass into the breast milk of nursing women taking progestin-only pills for long-term contraception, resulting in detectable steroid levels in infant plasma. (8.3)
- Levonorgestrel Tablet is not intended for use in premenarcheal (8.4) or postmenopausal females (8.5).

FULL PRESCRIBING INFORMATION

1 INDICATIONS & USAGE

Levonorgestrel Tablet, 1.5 mg is a progestin-only emergency contraceptive indicated for prevention of pregnancy following unprotected intercourse or a known or suspected contraceptive failure. To obtain optimal efficacy, the tablet should be taken as soon as possible within 72 hours of intercourse.

Levonorgestrel Tablet is available only by prescription for women younger than age 17 years, and available over the counter for women 17 years and older. Levonorgestrel Tablet is not indicated for routine use as a contraceptive.

2 DOSAGE & ADMINISTRATION

Take Levonorgestrel Tablet orally as soon as possible within 72 hours after unprotected intercourse or a known or suspected contraceptive failure. Efficacy is better if the tablet is taken as soon as possible after unprotected intercourse. Levonorgestrel Tablet can be used at any time during the menstrual cycle.

If vomiting occurs within two hours of taking the tablet, consideration should be given to repeating the dose.

3 DOSAGE FORMS & STRENGTHS

The Levonorgestrel Tablet is supplied as a white to off-white, round, flat tablets containing 1.5 mg of levonorgestrel and debossed with “NL 620” on one side and plain on the other side.

4 CONTRAINDICATIONS

Levonorgestrel Tablet is contraindicated for use in the case of known or suspected pregnancy.

5 WARNINGS AND PRECAUTIONS

5.1 Ectopic Pregnancy

Ectopic pregnancies account for approximately 2% of all reported pregnancies. Up to 10% of pregnancies reported in clinical studies of routine use of progestin-only contraceptives are ectopic.

A history of ectopic pregnancy is not a contraindication to use of this emergency contraceptive method. Healthcare providers, however, should consider the possibility of an ectopic pregnancy in women who become pregnant or complain of lower abdominal pain after taking Levonorgestrel Tablet. A follow-up physical or pelvic examination is recommended if there is any doubt concerning the general health or pregnancy status of any woman after taking Levonorgestrel Tablet.

5.2 Existing Pregnancy

Levonorgestrel tablet is not effective in terminating an existing pregnancy.

5.3 Effects on Menses

Some women may experience spotting a few days after taking Levonorgestrel Tablet. Menstrual bleeding patterns are often irregular among women using progestin-only oral contraceptives and women using levonorgestrel for postcoital and emergency contraception.

If there is a delay in the onset of expected menses beyond 1 week, consider the possibility of pregnancy.

5.4 STI/HIV

Levonorgestrel Tablet does not protect against HIV infection (AIDS) or other sexually transmitted infections (STIs).

5.5 Physical Examination and Follow-up

A physical examination is not required prior to prescribing Levonorgestrel Tablet. A follow-up physical or pelvic examination is recommended if there is any doubt concerning the general health or pregnancy status of any woman after taking Levonorgestrel Tablet.

5.6 Fertility Following Discontinuation

A rapid return of fertility is likely following treatment with Levonorgestrel Tablet for emergency contraception; therefore, routine contraception should be continued or initiated as soon as possible following use of Levonorgestrel Tablet to ensure ongoing prevention of pregnancy.

6 ADVERSE REACTIONS

6.1 Clinical Trials Experience

Because clinical trials are conducted under widely varying conditions, adverse reaction rates observed in the clinical trials of a drug cannot be directly compared to rates in the clinical trials of another drug and may not reflect the rates observed in clinical practice.

Levonorgestrel Tablet was studied in a randomized, double-blinded multicenter clinical trial. In this study, all women who had received at least one dose of study medication were included in the safety analysis: 1,379 women in the Levonorgestrel Tablet group, and 1,377 women in the Plan B group (2 doses of 0.75 mg levonorgestrel taken 12 hours apart). The mean age of women given Levonorgestrel Tablet was 27 years. The racial demographic of those enrolled was 54% Chinese, 12% Other Asian or Black, and 34% were Caucasian in each treatment group. 1.6% of women in the Levonorgestrel Tablet group and 1.4% in Plan B group were lost to follow-up.

The most common adverse events (>10%) in the clinical trial for women receiving Levonorgestrel Tablet included heavier menstrual bleeding (30.9%), nausea (13.7%), lower abdominal pain (13.3%), fatigue (13.3%), and headache (10.3%). Table 1 lists those adverse events that were reported in > 4% of Levonorgestrel Tablet users.

Most Common Adverse Events (MedDRA)
Heavier menstrual bleeding | 30.9
Nausea | 13.7
Lower abdominal pain | 13.3
Fatigue | 13.3
Headache | 10.3
Dizziness | 9.6
Breast tenderness | 8.2
Delay of menses (> 7 days) | 4.5

6.2 Postmarketing Experience

The following adverse reactions have been identified during post-approval use of Plan B (2 doses of 0.75 mg levonorgestrel taken 12 hours apart). Because these reactions are reported voluntarily from a population of uncertain size, it is not always possible to reliably estimate their frequency or establish a causal relationship to drug exposure.

Gastrointestinal Disorders

Abdominal Pain, Nausea, Vomiting

General Disorders and Administration Site Conditions

Fatigue

Nervous System Disorders

Dizziness, Headache

Reproductive System and Breast Disorders

Dysmenorrhea, Irregular Menstruation, Oligomenorrhea, Pelvic Pain

7 DRUG INTERACTIONS

Drugs or herbal products that induce enzymes, including CYP3A4, that metabolize progestins may decrease the plasma concentrations of progestins, and may decrease the effectiveness of progestin-only pills. Some drugs or herbal products that may decrease the effectiveness of progestin-only pills include:

- Barbiturates
- bosentan
- carbamazepine
- felbamate
- griseofulvin
- oxcarbazepine
- phenytoin
- rifampin
- St. John’s wort
- topiramate

Significant changes (increase or decrease) in the plasma levels of the progestin have been noted in some cases of co-administration with HIV protease inhibitors or with non-nucleoside reverse transcriptase inhibitors.

Consult the labeling of all concurrently used drugs to obtain further information about interactions with progestin-only pills or the potential for enzyme alterations.

8 USE IN SPECIFIC POPULATIONS

8.1 Pregnancy

Many studies have found no harmful effects on fetal development associated with long-term use of contraceptive doses of oral progestins. The few studies of infant growth and development that have been conducted with progestin-only pills have not demonstrated significant adverse effects.

8.3 Nursing Mothers

In general, no adverse effects of progestin-only pills have been found on breastfeeding performance or on the health, growth, or development of the infant. However, isolated post-marketing cases of decreased milk production have been reported. Small amounts of progestins pass into the breast milk of nursing mothers taking progestin-only pills for long-term contraception, resulting in detectable steroid levels in infant plasma.

8.4 Pediatric Use

Safety and efficacy of progestin-only pills for long-term contraception have been established in women of reproductive age. Safety and efficacy are expected to be the same for postpubertal adolescents less than 17 years and for users 17 years and older. Use of Levonorgestrel Tablet emergency contraception before menarche is not indicated.

8.5 Geriatric Use

This product is not intended for use in postmenopausal women.

8.6 Race

No formal studies have evaluated the effect of race. However, clinical trials demonstrated a higher pregnancy rate in Chinese women with both Plan B and the Yuzpe regimen (another form of emergency contraception). There was a non-statistically significant increased rate of pregnancy among Chinese women in the Levonorgestrel Tablet trial. The reason for this apparent increase in the pregnancy rate with emergency contraceptives in Chinese women is unknown.

8.7 Hepatic Impairment

No formal studies were conducted to evaluate the effect of hepatic disease on the disposition of Levonorgestrel Tablet.

8.8 Renal Impairment

No formal studies were conducted to evaluate the effect of renal disease on the disposition of Levonorgestrel Tablet.

9 DRUG ABUSE AND DEPENDENCE

Levonorgestrel is not a controlled substance. There is no information about dependence associated with the use of Levonorgestrel Tablet.

10 OVERDOSAGE

There are no data on overdosage of Levonorgestrel Tablet, although the common adverse event of nausea and associated vomiting may be anticipated.

11 DESCRIPTION

Levonorgestrel Tablet contains 1.5 mg of a single active steroid ingredient, levonorgestrel [18,19-Dinorpregn-4-en-20-yn-3-one-13-ethyl-17-hydroxy-, (17α)-(-)-], a totally synthetic progestogen. The inactive ingredients are colloidal silicon dioxide, pregelatinized starch, lactose monohydrate, magnesium stearate, and talc.

Levonorgestrel has a molecular weight of 312.45, and the following structural and molecular formulas:

12 CLINICAL PHARMACOLOGY

12.1 Mechanism of Action

Emergency contraceptive pills are not effective if a woman is already pregnant. Levonorgestrel Tablet is believed to act as an emergency contraceptive principally by preventing ovulation or fertilization (by altering tubal transport of sperm and/or ova). In addition, it may inhibit implantation (by altering the endometrium). It is not effective once the process of implantation has begun.

12.3 Pharmacokinetics

Absorption

Following a single dose administration of Levonorgestrel Tablet in 30 women under fasting conditions, maximum plasma concentrations of levonorgestrel of 19.1 ng/mL were reached at 1.7 hours. See Table 2.

Administration of Levonorgestrel tablet to 30 Healthy Female Volunteers under Fasting Conditions[/TC]

Mean (± SD)
Cmax(ng/mL) | AUCt(ng·hr/mL)* | AUCinf(ng·hr/mL)*
 | Tmax(hr)** | t1/2 (hr)
Levonorgestrel | 19.1 (9.7) | 294.8(208.8) | 307.5(218.5) | 1.7(1.0-4.0) | 27.5(5.6)

Cmax = maximum concentration

AUCt = area under the drug concentration curve from time 0 to time of last determinable concentration

AUCinf = area under the drug concentration curve from time 0 to infinity

Tmax = time to maximum concentration

t1/2= elimination half life

* N=29

** median (range)

Effect of Food: The effect of food on the rate and the extent of levonorgestrel absorption following single oral administration of Levenorgestrel Tablet has not been evaluated.

Distribution

The apparent volume of distribution of levonorgestrel is reported to be approximately 1.8 L/kg. It is about 97.5 to 99% protein-bound, principally to sex hormone binding globulin (SHBG) and, to a lesser extent, serum albumin.

Metabolism

Following absorption, levonorgestrel is conjugated at the 17β-OH position to form sulfate conjugates and, to a lesser extent, glucuronide conjugates in plasma. Significant amounts of conjugated and unconjugated 3α, 5β-tetrahydrolevonorgestrel are also present in plasma, along with much smaller amounts of 3α, 5α-tetrahydrolevonorgestrel and 16βhydroxylevonorgestrel. Levonorgestrel and its phase I metabolites are excreted primarily as glucuronide conjugates. Metabolic clearance rates may differ among individuals by several-fold, and this may account in part for the wide variation observed in levonorgestrel concentrations among users.

Excretion

About 45% of levonorgestrel and its metabolites are excreted in the urine and about 32% are excreted in feces, mostly as glucuronide conjugates.

Specific Populations

Pediatric

This product is not intended for use in the premenarcheal population, and pharmacokinetic data are not available for this population.

Geriatric

This product is not intended for use in postmenopausal women, and pharmacokinetic data are not available for this population.

Race

No formal studies have evaluated the effect of race. However, clinical trials demonstrated a higher pregnancy rate in Chinese women with both Plan B and the Yuzpe regimen (another form of emergency contraception). There was a non-statistically significant increased rate of pregnancy among Chinese women in the Levonorgestrel Tablet trial. The reason for this apparent increase in the pregnancy rate with emergency contraceptives in Chinese women is unknown [see USE IN SPECIFIC POPULATIONS (8.6)].

Hepatic Impairment

No formal studies were conducted to evaluate the effect of hepatic disease on the disposition of Levonorgestrel Tablet.

Renal Impairment

No formal studies were conducted to evaluate the effect of renal disease on the disposition of Levonorgestrel Tablet.

Drug-Drug Interactions

No formal drug-drug interaction studies were conducted with Levonorgestrel Tablet [see DRUG INTERACTIONS (7)].

13 NONCLINICAL TOXICOLOGY

13.1 Carcinogenesis, Mutagenesis, Impairment of Fertility

Carcinogenicity: There is no evidence of increased risk of cancer with short-term use of progestins. There was no increase in tumorgenicity following administration of levonorgestrel to rats for 2 years at approximately 5 µg/day, to dogs for 7 years at up to 0.125 mg/kg/day, or to rhesus monkeys for 10 years at up to 250 µg/kg/day. In another 7 year dog study, administration of levonorgestrel at 0.5 mg/kg/day did increase the number of mammary adenomas in treated dogs compared to controls. There were no malignancies.

Genotoxicity: Levonorgestrel was not found to be mutagenic or genotoxic in the Ames Assay, in vitro mammalian culture assays utilizing mouse lymphoma cells and Chinese hamster ovary cells, and in an in vivo micronucleus assay in mice.

Fertility: There are no irreversible effects on fertility following cessation of exposures to levonorgestrel or progestins in general.

14 CLINICAL STUDIES

A double-blind, randomized, multicenter, multinational study evaluated and compared the efficacy and safety of three different regimens for emergency contraception. Subjects were enrolled at 15 sites in 10 countries; the racial/ethnic characteristics of the study population overall were 54% Chinese, 34% Caucasian, and 12% Black or Asian (other than Chinese). 2,381 healthy women with a mean age of 27 years, who needed emergency contraception within 72 hours of unprotected intercourse were involved and randomly allocated into one of the two levonorgestrel groups. A single dose of 1.5 mg of levonorgestrel was administered to women allocated into group 1. Two doses of 0.75 mg levonorgestrel 12 hours apart (Plan B) were administered to women in group 2. In the Levonorgestrel Tablet, 1.5 mg group, 16 pregnancies occurred in 1,198 women and in the Plan B group, 20 pregnancies occurred in 1,183 women. The number of pregnancies expected in each group was calculated based on the timing of intercourse with regard to each woman’s menstrual cycle. Among women receiving Levonorgestrel Tablet, 1.5 mg 84% of expected pregnancies were prevented and among those women taking Plan B, 79% of expected pregnancies were prevented. The expected pregnancy rate of 8% (with no contraceptive use) was reduced to approximately 1% with Levonorgestrel Tablet, 1.5 mg.

Emergency contraceptives are not as effective as routine contraception since their failure rate, while low based on a single use, would accumulate over time with repeated use [see INDICATIONS AND USAGE (1)].

In the clinical study, bleeding disturbances were the most common adverse event reported after taking the levonorgestrel-containing regimens. More than half of the women had menses within two days of the expected time; however, 31% of women experienced change in their bleeding pattern during the study period; 4.5% of women had menses more than 7 days after the expected time.

16 HOW SUPPLIED/STORAGE AND HANDLING

Levonorgestrel Tablet, 1.5 mg is available in a PVC/aluminum foil blister package. The tablet is a white to off-white, round, flat, debossed with “NL 620” on one side and plain on the other side containing 1.5 mg of levonorgestrel.

NDC 63704-009-01 (1 tablet unit of use package)

Store Levonorgestrel Tablet at 20° to 25°C (68° to 77°F) [see USP Controlled Room Temperature].

17 PATIENT COUNSELING INFORMATION

17.1 Information for Patients

- Take Levonorgestrel Tablets as soon as possible and not more than 72 hours after unprotected intercourse or a known or suspected contraceptive failure.
- If you vomit within two hours of taking the tablet, immediately contact your healthcare provider to discuss whether to take another tablet.
- Seek medical attention if you experience severe lower abdominal pain 3 to 5 weeks after taking Levonorgestrel Tablet, in order to be evaluated for an ectopic pregnancy.
- After taking Levonorgestrel Tablet, consider the possibility of pregnancy if your period is delayed more than one week beyond the date you expected your period.
- Do not use Levonorgestrel Tablet as routine contraception.
- Levonorgestrel Tablet is not effective in terminating an existing pregnancy.
- Levonorgestrel Tablet does not protect against HIV-infection (AIDS) and other sexually transmitted diseases/infections.
- For women younger than age 17 years, Levonorgestrel Tablet is available only by prescription.

Mfg. for:

Pharmacist Pharmaceutical, LLC

Salem, VA 24153

PI6203003501 Iss. April 2013

Medication Guide

Levonorgestrel Tablet, 1.5 mg

Emergency Contraceptive

Because the unexpected happens.

Important information about Levonorgestrel Tablets,

Birth Control and Sexually Transmitted Diseases

For additional information intended for healthcare professionals, please see enclosed Product Information for Levonorgestrel Tablet.

What is Levonorgestrel Tablet?

Levonorgestrel Tablet is emergency contraception that helps prevent pregnancy after birth control failure or unprotected sex. It is a backup method of preventing pregnancy and is not to be used routinely.

Levonorgestrel Tablet can reduce your chance of pregnancy after unprotected sex (if your regular birth control was used incorrectly or fails, or if you have had sex without birth control). For example, if you were using a condom and it broke or slipped, if you did not use your regular birth control as you should have, or if you did not use any birth control, Levonorgestrel Tablet may work for you.

What Levonorgestrel Tablet is not.

Levonorgestrel Tablet will not work if you are already pregnant and will not affect an existing pregnancy. Levonorgestrel Tablet should not be used as regular birth control. It is important to have another reliable source of birth control that is right for you. Levonorgestrel Tablet will not protect you from HIV infection (the virus that causes AIDS) and other sexually transmitted diseases.

When is the appropriate time to use Levonorgestrel Tablet?

You can use Levonorgestrel Tablet after you have had unprotected sex in the last 72 hours (3 days), and you do not want to become pregnant.

Levonorgestrel Tablet can be used as a backup or emergency method to regular birth control if, for example,

- Your regular birth control method was used incorrectly or failed (your partner’s condom broke or slipped)
- You made a mistake with your regular method
- You did not use any birth control method

When is it not appropriate to use Levonorgestrel Tablet?

- Levonorgestrel Tablet should not be used as a regular birth control method. It does not work as well as most other forms of birth control when they are used consistently and correctly. Levonorgestrel Tablet is a backup or emergency method of contraception.
- Levonorgestrel Tablet should not be used if you are already pregnant because it will not work.
- Levonorgestrel Tablet should not be used if you are allergic to levonorgestrel or any other ingredients in Levonorgestrel Tablet.
- Levonorgestrel Tablet does not protect against HIV (the virus that causes AIDS) or other sexually transmitted diseases (STDs). The best ways to protect yourself against getting HIV or other STDs are to use a latex condom correctly with every sexual act or not to have sex at all.

How does Levonorgestrel Tablet work?

Levonorgestrel Tablet is one pill with levonorgestrel, a hormone that has been used in many birth control pills for over 35 years. Levonorgestrel Tablet contains a higher dose of levonorgestrel than birth control pills, but works in a similar way to prevent pregnancy. It works mainly by stopping the release of an egg from the ovary. It is possible that Levonorgestrel Tablet may also work by preventing fertilization of an egg (the uniting of sperm with the egg) or by preventing attachment (implantation) to the uterus (womb).

How can I get the best results from Levonorgestrel Tablet?

You have only a few days to try to prevent pregnancy after unprotected sex. The sooner you take Levonorgestrel Tablet, the better it works. Levonorgestrel Tablet should be taken as soon as possible within 72 hours (3 days) after unprotected sex.

How effective is Levonorgestrel Tablet?

The sooner you take Levonorgestrel Tablet, the better it will work. Take Levonorgestrel Tablet as soon as possible after unprotected sex. If it is taken as soon as possible within 72 hours (3 days) after unprotected sex, it will significantly decrease the chance that you will get pregnant. Seven out of every 8 women who would have gotten pregnant will not become pregnant.

How will I know if Levonorgestrel Tablet worked?

Most women will have their next menstrual period at the expected time or within a week of the expected time. If your menstrual period is delayed beyond 1 week, you may be pregnant. You should get a pregnancy test and follow up with your healthcare professional.

What if I am already pregnant and use Levonorgestrel Tablet?

There is no medical evidence that Levonorgestrel Tablet would harm a developing baby. If you take Levonorgestrel Tablet (accidentally) after you are already pregnant or it does not work and you become pregnant, it is not likely to cause any harm to you or your pregnancy. The pregnancy will continue. Levonorgestrel Tablet will not work if you are already pregnant.

What should I do if my menstrual period is delayed beyond 1 week and I have severe lower stomach (abdominal) pain?

If you have severe lower stomach (abdominal) pain about 3 to 5 weeks after taking Levonorgestrel Tablet, you may have a pregnancy outside the uterus, which is called a tubal pregnancy. A tubal pregnancy requires immediate medical treatment, so you should see a healthcare professional right away.

Can I use Levonorgestrel Tablet for regular birth control?

No. Levonorgestrel Tablet should not be used for regular birth control. It is an emergency or backup method to be used if your regular birth control fails or is used incorrectly or if you have sex without birth control. You should protect yourself against STDs and pregnancy every time you have sex. If you have unprotected sex again after taking Levonorgestrel Tablet, it will not help protect you from getting pregnant.

How often can I use Levonorgestrel Tablet?

Levonorgestrel Tablet is meant for emergency protection only, and is not designed to be used frequently. If you find that you need to use emergency contraception often, talk to your healthcare professional and learn about methods of birth control and STD prevention that are right for you.

Will I experience any side effects from Levonorgestrel Tablet?

When used as directed, Levonorgestrel Tablet is safe for women. Some women will have mild, temporary side effects, such as menstrual changes, nausea, lower stomach (abdominal) pain, tiredness, headache, dizziness, breast pain and vomiting. These are similar to the side effects that some women have when taking regular birth control pills. Some women taking Levonorgestrel Tablet will have menstrual changes such as spotting or bleeding before their next period. Some women may have a heavier or lighter next period, or a period that is early or late. If your period is more than a week late, you should get a pregnancy test.

What warnings should I know about when using Levonorgestrel Tablet?

Levonorgestrel Tablet does not protect against AIDS virus (HIV) or other sexually transmitted diseases (STDs).

Do not use:

- If you are already pregnant (because it will not work)
- If you are allergic to levonogestrel or any of the ingredients in Levonorgestrel Tablet
- For regular birth control

When using this product, you may have:

- Menstrual changes
- Headache
- Nausea
- Dizziness
- Lower stomach (abdominal) pain
- Breast pain
- Tiredness
- Vomiting

Keep out of reach of children.

In case of overdose, get medical help or contact a Poison Control Center right away at 1-800-222-1222.

What are the directions for using Levonorgestrel Tablet?

Women 17 years of age and older:

- Take Levonorgestrel Tablet as soon as possible within 72 hours (3 days) after unprotected sex.
- If you vomit within 2 hours of taking the medication, call a healthcare professional to find out if you should repeat the dose.

Prescription only for women younger than age 17. If you are younger than age 17, see a healthcare professional.

What should I do if I have questions about Levonorgestrel Tablet?

If you have questions or need more information about this product, call our toll-free number, 1-800-224-4606, visit our website at www.ecpill.com, or ask a healthcare professional.

Other information

Tablet is enclosed in a blister seal. Do not use if the blister seal is broken.

Store at room temperature 20–25°C (68–77°F).

You may report side effects to FDA at 1-800-FDA-1088.

Active ingredient: Levonorgestrel 1.5 mg

Inactive ingredients: colloidal silicon dioxide, pregelatinized starch, magnesium stearate, talc, and lactose monohydrate

Protect yourself in more ways than one!

If you are sexually active, but you are not ready for a pregnancy, it is important to use regular pregnancy protection. There are many types of birth control. Whichever type you choose, it is important to use your regular birth control method as directed. This ensures that you have effective protection against pregnancy every time you have sex.

But things do not always go as planned. For example, if you were using a condom and it broke or slipped, or if you did not use your regular birth control as you should have, or if you did not use any birth control, Levonorgestrel Tablet may work for you. Levonorgestrel Tablet is an emergency contraceptive that helps prevent pregnancy after unprotected sex or when your birth control fails or is not used correctly.

Remember, Levonorgestrel Tablet is only for emergency pregnancy prevention. There are many other products that work for regular birth control that are available by prescription or over-the-counter.

There is also another form of protection to think about when you have sex: protection against sexually transmitted diseases (STDs). Some common STDs are HIV/AIDS, chlamydia, genital herpes, gonorrhea, hepatitis, human papilloma virus (HPV), genital warts, syphilis, and trichomonas. Some of these STDs can be very serious and can lead to infertility (inability to have a baby), problems during pregnancy, chronic illness, and even death.

All sexually active women are at risk of catching STDs because they may not know that their partner has an STD (the partner himself may not know). If your partner uses a latex condom correctly each and every time you have sex with him, this will help reduce, but not eliminate, the chance that you will catch an STD.

No other birth control methods will effectively protect you from STDs. The female condom may give you some STD protection, but it is not as effective as a male latex condom.

For more information on STDs, call the Centers for Disease Control and Prevention (CDC) AIDS/STD Hotline. The CDC phone numbers are 1-800-342-AIDS (2437) for English, 1-800-344-7432 for Spanish, or 1-800-243-7889 for hearing impaired, TDD.

Be sure to protect yourself against pregnancy and STDs by using some form of birth control plus a latex condom. Of course, not having sex is the most effective way to prevent pregnancy and stay free of STDs

Levonorgestrel Tablet is used to prevent pregnancy after unprotected sex.

Levonorgestrel Tablet should not be used for regular birth control, if you are already pregnant (because it will not work), or if you are allergic to levonorgestrel or any of the ingredients in Levonorgestrel Tablet.

The sooner you take Levonorgestrel Tablet the better it will work.

Levonorgestrel Tablet does not protect against the AIDS virus (HIV) or other sexually transmitted diseases (STDs)

Common side effects associated with the use of Levonorgestrel Tablet include menstrual changes, nausea, lower stomach (abdominal) pain, tiredness, headache, dizziness, breast pain and vomiting.

PACKAGE LABEL.PRINCIPAL DISPLAY PANEL

NDC 63704-009-01

Levonorgestrel Tablet, 1.5 mg

Emergency Contraceptive